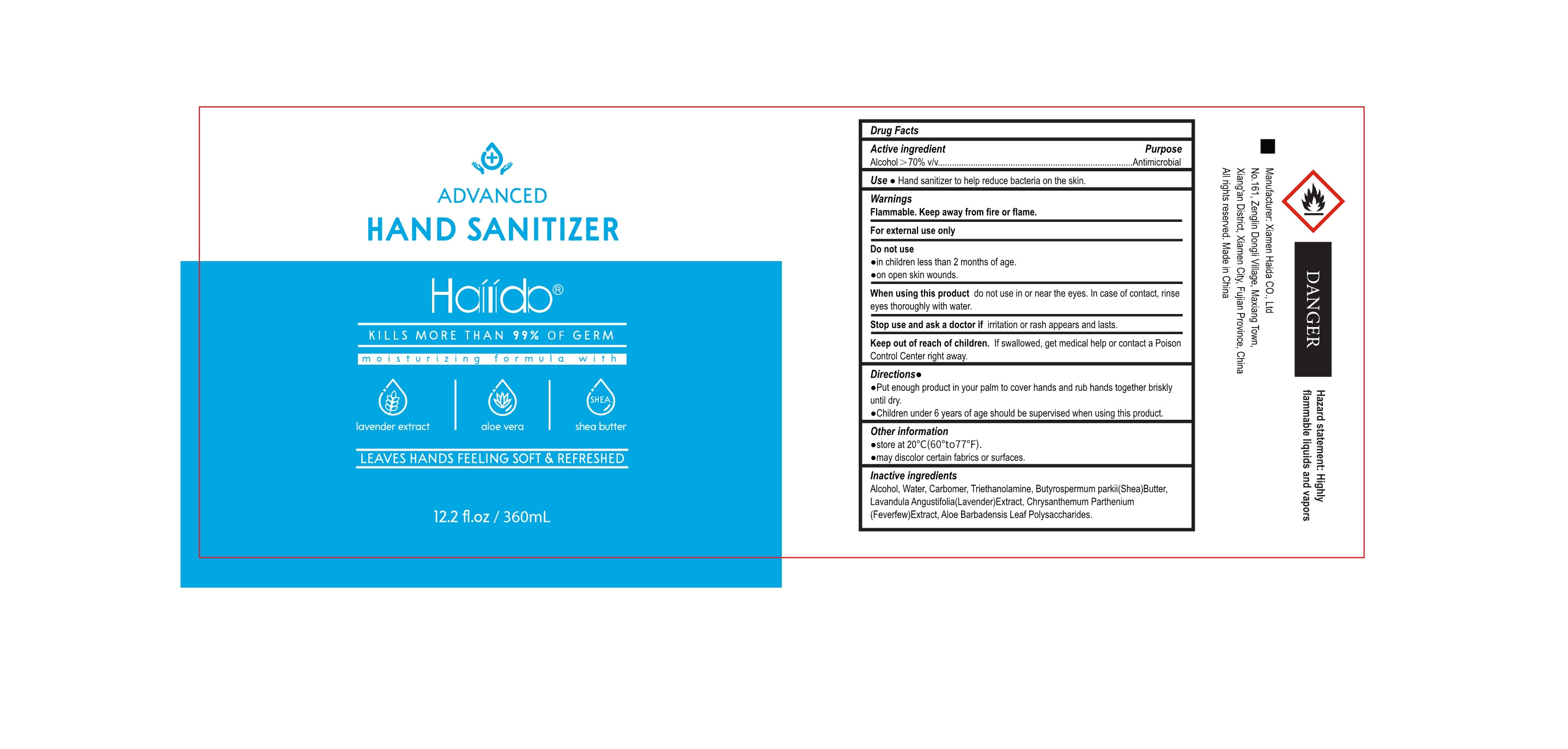 DRUG LABEL: HAND SANITIZER
NDC: 52897-008 | Form: LIQUID
Manufacturer: Xiamen Haida Co., Ltd
Category: otc | Type: HUMAN OTC DRUG LABEL
Date: 20200720

ACTIVE INGREDIENTS: ALCOHOL 253.8 mL/360 mL
INACTIVE INGREDIENTS: CARBOMER HOMOPOLYMER, UNSPECIFIED TYPE; TROLAMINE; TANACETUM PARTHENIUM; WATER; SHEA BUTTER; LAVANDULA ANGUSTIFOLIA FLOWERING TOP; ALOE VERA LEAF POLYSACCHARIDES

DOSAGE AND ADMINISTRATION

store at 20°C(60°to77*F).

INACTIVE INGREDIENT

Water

Carbomer

Triethanolamine

Butyrospermum parkii(Shea) Butter

Lavandula Angustifolia(Lavender) Extract

Chrysanthemum Parthenium (Feverfew)Extract

Aloe Barbadensis Leaf Polysaccharides

INDICATIONS AND USAGE

Put enough product in your palm to cover hands and rub hands together briskly.

ACTIVE INGREDIENT

Alcohol

keep out of children

PURPOSE

Disinfection
Sterilization
No Rinseing

WARNINGS

Flammable.Keep away from fire or flame.For external use only.